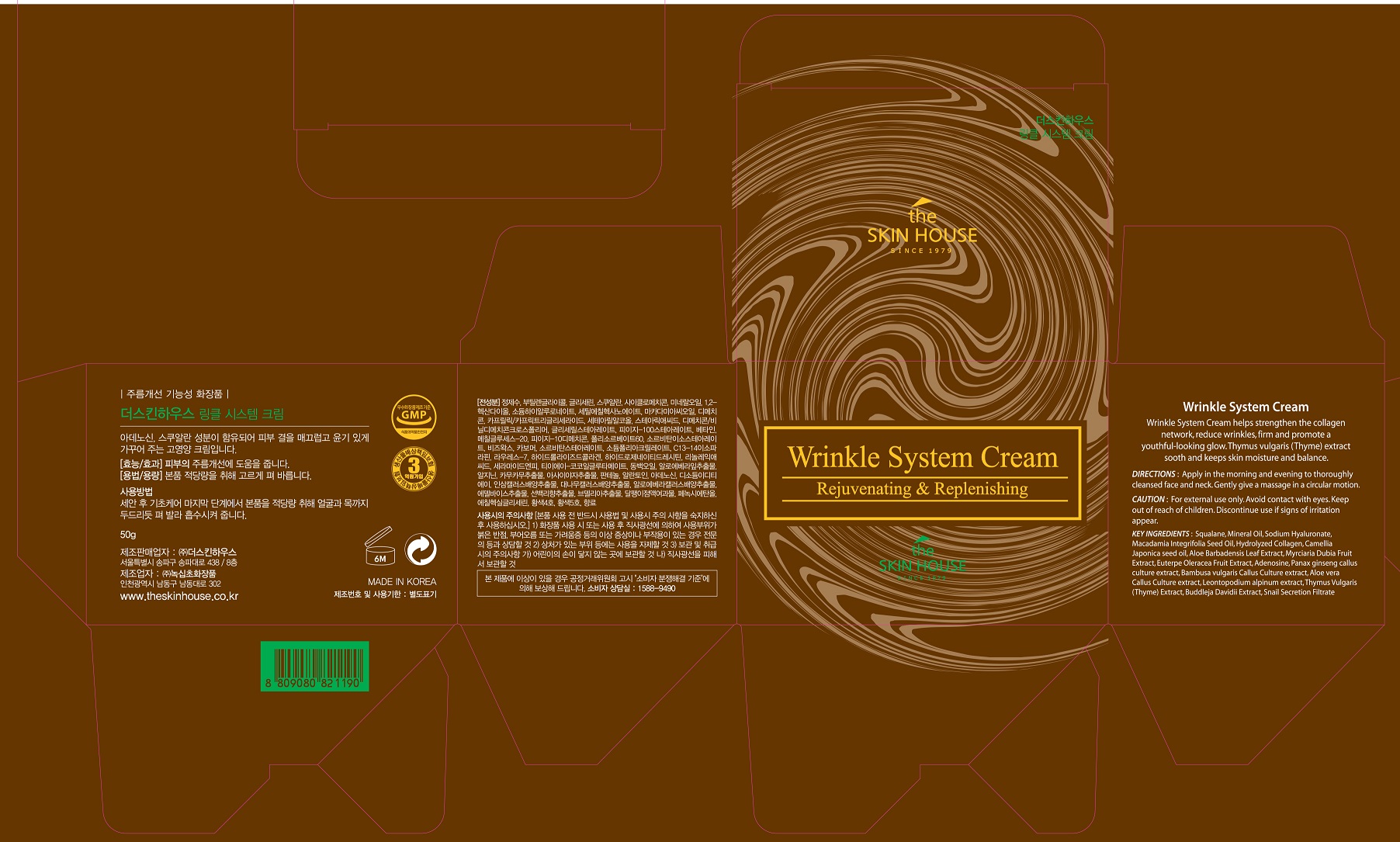 DRUG LABEL: THE SKIN HOUSE Wrinkle SystemCream
NDC: 73590-0033 | Form: CREAM
Manufacturer: NOKSIBCHO cosmetic Co., Ltd.
Category: otc | Type: HUMAN OTC DRUG LABEL
Date: 20200331

ACTIVE INGREDIENTS: ADENOSINE 0.04 g/100 g
INACTIVE INGREDIENTS: WATER

Drug Facts

ACTIVE INGREDIENT

adenosine

INACTIVE INGREDIENT

Water
Butylene glycol
Glycerin
Squalane
Cyclomethicone
Mineral Oil
Dimethicone
1,2-Hexanediol
Sodium Hyaluronate
Cetyl Ethylhexanoate
Macadamia Integrifolia Seed Oil
Caprylic/Capric Triglyceride
Cetearyl Alcohol
Stearic Acid
Dimethicone/Vinyl Dimethicone Crosspolymer
PEG-100 Stearate
Betaine
Methyl Gluceth-20
PEG-10 Dimethicone
Polysorbate 60
Sorbitan Isostearate
Beeswax
Glyceryl Stearate
Carbomer
Sorbitan Stearate
Sodium Polyacrylate
C13-14 Isoparaffin
Laureth-7
Hydrolyzed Collagen
Hydrogenated Lecithin
Linoleic acid
Water
Ceramide NP
TEA-cocoyl Glutamate
Camellia Japonica seed oil
Aloe Barbadensis Leaf Extract
Arginine
Myrciaria Dubia Fruit Extract
Euterpe Oleracea Fruit Extract
Panthenol
Allantoin
Disodium EDTA
Panax ginseng callus culture extract
Bambusa vulgaris Callus Culture extract
Aloe vera Callus Culture extract
Leontopodium alpinum extract
Thymus Vulgaris (Thyme) Extract
Buddleja Davidii Extract
Snail Secretion Filtrate
Phenoxyethanol
Ethylhexylglycerin
CI 19140
CI 15985
Parfume

PURPOSE

wrinkle care

keep out of reach of the children

INDICATIONS AND USAGE

apply proper amount to the skin

WARNINGS

For external use only
When using this product

■ if the following symptoms occurs after use, stop use and consult with a skin specialist

red specks, swelling, itching

■ don’t use on the part where there is injury, eczema, or dermatitis

Keep out of reach of children

■ if swallowed, get medical help or contact a person control center immediately